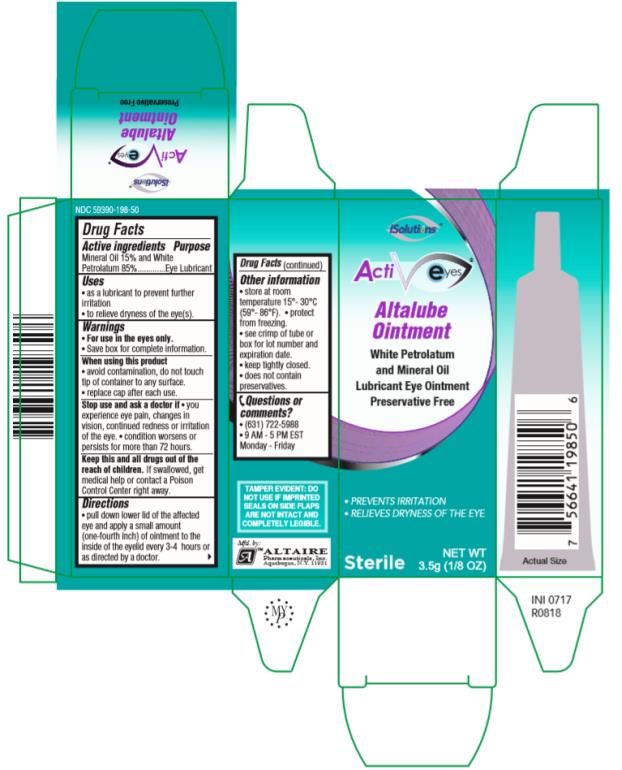 DRUG LABEL: Altalube
NDC: 59390-198 | Form: OINTMENT
Manufacturer: Altaire Pharmaceuticals Inc.
Category: otc | Type: HUMAN OTC DRUG LABEL
Date: 20231209

ACTIVE INGREDIENTS: MINERAL OIL 150 mg/1 g; PETROLATUM 850 mg/1 g
INACTIVE INGREDIENTS: LANOLIN ALCOHOLS

Altalube Ointment

ActivEyes

Altalube Ointment 3.5g

NDC 59390-198-50

Drug Facts

Active ingredients

Mineral Oil 15% and White Petrolatum 85%

Purpose

Eye Lubricant

Uses

• as a lubricant to prevent further irritation • to relieve dryness of the eye(s).

Warnings

• Save box for complete information. • For use in the eyes only.

When using this product

• avoid contamination, do not touch tip of container to any surface.

• replace cap after each use.

Stop use and ask a doctor if

• you experience eye pain, changes in vision, continued redness or irritation of the eye. • condition worsens or persists for more than 72 hours.

Keep this and all drugs out of the reach of children.

If swallowed, get medical help or contact a Poison Control Center right away.

Directions

• pull down lower lid of the affected eye and apply a small amount (one-fourth inch) of ointment to the inside of the eyelid every 3-4 hours or as directed by a doctor.

Other information

• store at room temperature 15°-30°C (59°-86°F). • protect from freezing.

• see crimp of tube or box for lot number and expiration date.

• keep tightly closed.

• does not contain preservatives.

Inactive Ingredients

None remove

Questions or comments?

• (631) 722-5988• 9AM – 5 PM EST Monday- Friday

PRINCIPAL DISPLAY PANEL

ActiEyes Altalube OintmentWhite Petrolatum and Mineral OilLubricant Eye Ointment Preservative FreeSterileNET WT3.5g (1/8 OZ)